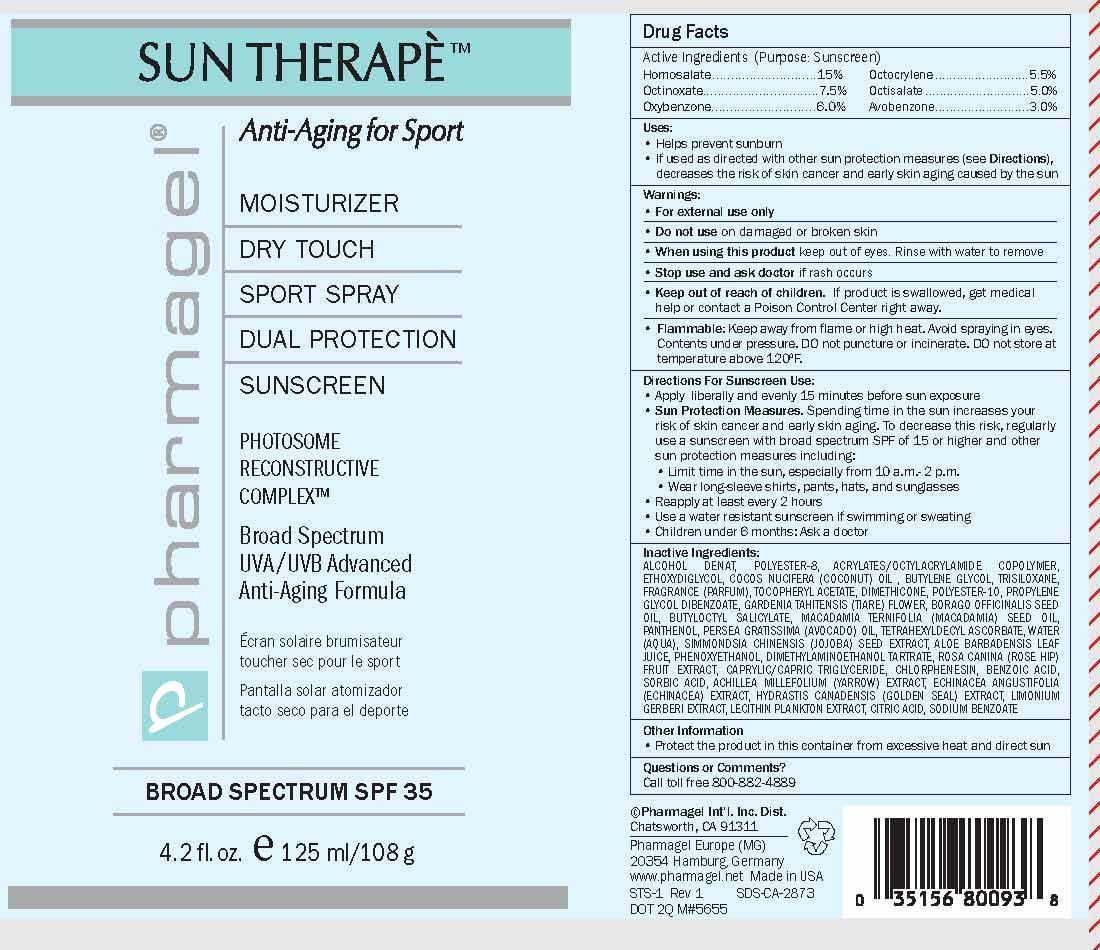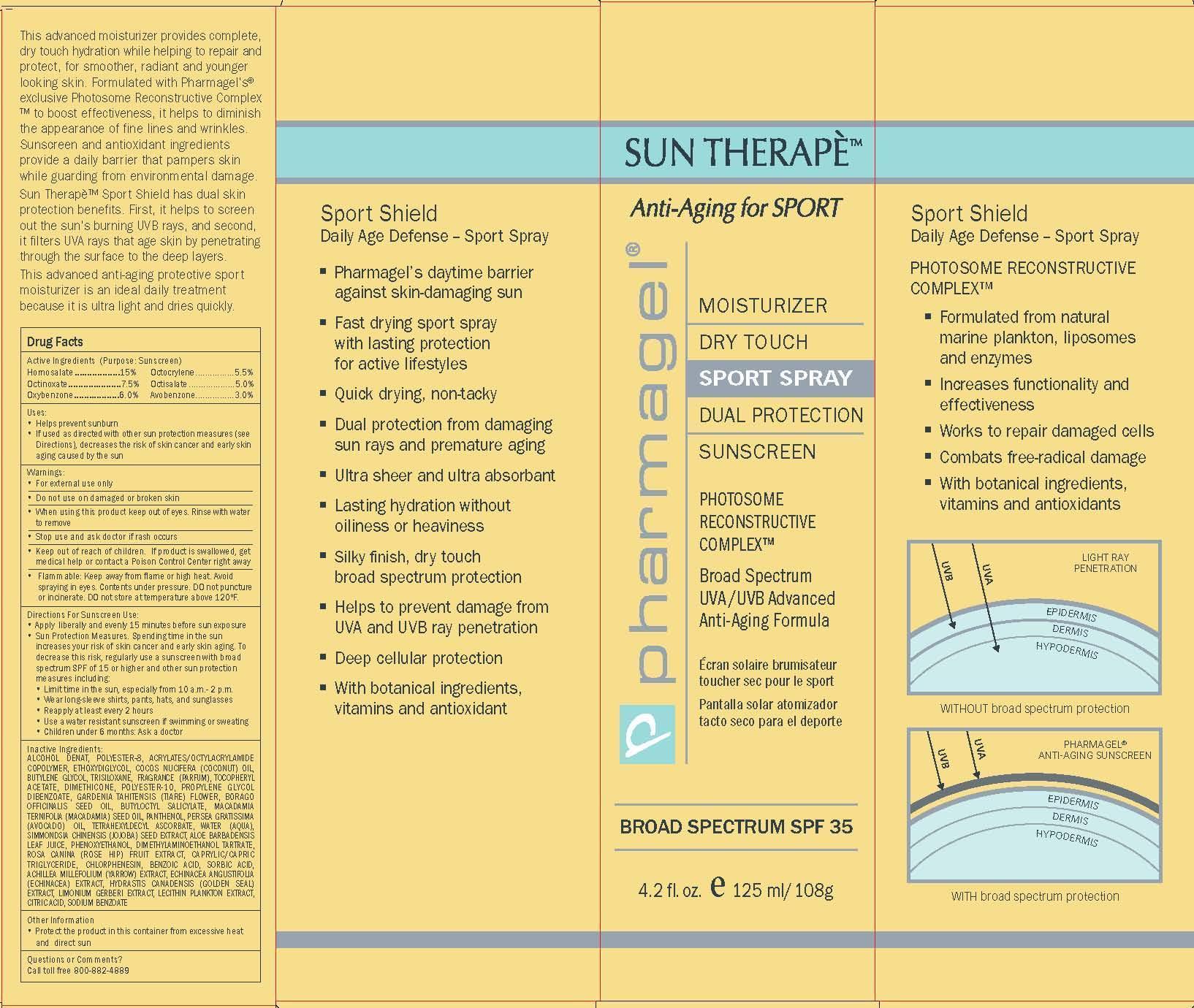 DRUG LABEL: SUN THERAPE SPORT

NDC: 67879-304 | Form: SPRAY
Manufacturer: PHARMAGEL INTERNATIONAL INC
Category: otc | Type: HUMAN OTC DRUG LABEL
Date: 20240813

ACTIVE INGREDIENTS: OXYBENZONE 6 g/100 mL; OCTOCRYLENE 5.5 g/100 mL; OCTISALATE 5 g/100 mL; AVOBENZONE 3 g/100 mL; HOMOSALATE 15 g/100 mL; OCTINOXATE 7.5 g/100 mL
INACTIVE INGREDIENTS: ECHINACEA ANGUSTIFOLIA; HYDRASTIS CANADENSIS WHOLE; LIMONIUM GERBERI WHOLE; LECITHIN, SOYBEAN; CHONDRUS CRISPUS; ANHYDROUS CITRIC ACID; SODIUM BENZOATE; ALCOHOL; POLYESTER-8 (1400 MW, CYANODIPHENYLPROPENOYL CAPPED); OCTYL ACRYLATE; DIETHYLENE GLYCOL MONOETHYL ETHER; COCONUT OIL; BUTYLENE GLYCOL; TRISILOXANE; .ALPHA.-TOCOPHEROL ACETATE; DIMETHICONE; POLYESTER-10; PROPYLENE GLYCOL DIBENZOATE; GARDENIA TAITENSIS FLOWER; BORAGO OFFICINALIS SEED; BUTYLOCTYL SALICYLATE; MACADAMIA OIL; PANTHENOL; AVOCADO OIL; TETRAHEXYLDECYL ASCORBATE; WATER; SIMMONDSIA CHINENSIS SEED; ALOE VERA LEAF; PHENOXYETHANOL; DEANOL BITARTRATE; ROSA CANINA FRUIT; MEDIUM-CHAIN TRIGLYCERIDES; CHLORPHENESIN; BENZOIC ACID; SORBIC ACID; ACHILLEA MILLEFOLIUM

PHARMAGEL - SUN THERAPE SPORT SPRAY (67879-304)

ACTIVE INGREDIENTS

Homosalate..................15%
Octinoxate.....................7.5%
Oxybenzone..................6.0%

Octocrylene................5.5%
Octisalate ...................5.0%
Avobenzone................3.0%

PURPOSE

SUNSCREEN

USES

• Helps prevent sunburn
• If used as directed with other sun protection measures (see Directions), decreases the risk of skin cancer and early skin aging caused by the sun

WARNINGS

• For external use only
• Do not use on damaged or broken skin
• When using this product keep out of eyes. Rinse with water to remove
• Stop use and ask doctor if rash occurs

• Keep out of reach of children. If product is swallowed, get medical help or contact a Poison Control Center right away.

OTHER SAFETY INFORMATION

• Flammable: Keep away from flame or high heat. Avoid spraying in eyes. Contents under pressure. DO not puncture or incinerate. DO not store at temperature above 120ºF.

Other Information
• Protect the product in this container from excessive heat
and direct sun

Directions For Sunscreen Use:

• Apply liberally and evenly 15 minutes before sun exposure
• Sun Protection Measures. Spending time in the sun increases your risk of skin cancer and early skin aging. To decrease this risk, regularly use a sunscreen with broad spectrum SPF of 15 or higher and other sun protection measures including:
• Limit time in the sun, especially from 10 a.m.- 2 p.m.
• Wear long-sleeve shirts, pants, hats, and sunglasses
• Reapply at least every 2 hours
• Use a water resistant sunscreen if swimming or sweating
• Children under 6 months: Ask a doctor

INACTIVE INGREDIENTS:

ALCOHOL DENAT, POLYESTER-8, ACRYLATES/OCTYLACRYLAMIDE COPOLYMER, ETHOXYDIGLYCOL, COCOS NUCIFERA (COCONUT) OIL, BUTYLENE GLYCOL, TRISILOXANE, FRAGRANCE (PARFUM), TOCOPHERYL ACETATE, DIMETHICONE, POLYESTER-10, PROPYLENE GLYCOL DIBENZOATE, GARDENIA TAHITENSIS (TIARE) FLOWER, BORAGO OFFICINALIS SEED OIL, BUTYLOCTYL SALICYLATE, MACADAMIA TERNIFOLIA (MACADAMIA) SEED OIL, PANTHENOL, PERSEA GRATISSIMA (AVOCADO) OIL, TETRAHEXYLDECYL ASCORBATE, WATER (AQUA), SIMMONDSIA CHINENSIS (JOJOBA) SEED EXTRACT, ALOE BARBADENSIS LEAF JUICE, PHENOXYETHANOL, DIMETHYLAMINOETHANOL TARTRATE, ROSA CANINA (ROSE HIP) FRUIT EXTRACT, CAPRYLIC/CAPRIC TRIGLYCERIDE, CHLORPHENESIN, BENZOIC ACID, SORBIC ACID, ACHILLEA MILLEFOLIUM (YARROW) EXTRACT, ECHINACEA ANGUSTIFOLIA (ECHINACEA) EXTRACT, HYDRASTIS CANADENSIS (GOLDEN SEAL) EXTRACT, LIMONIUM GERBERI EXTRACT, LECITHIN PLANKTON EXTRACT, CITRIC ACID, SODIUM BENZOATE

Questions or Comments?

Call toll free 800-882-4889